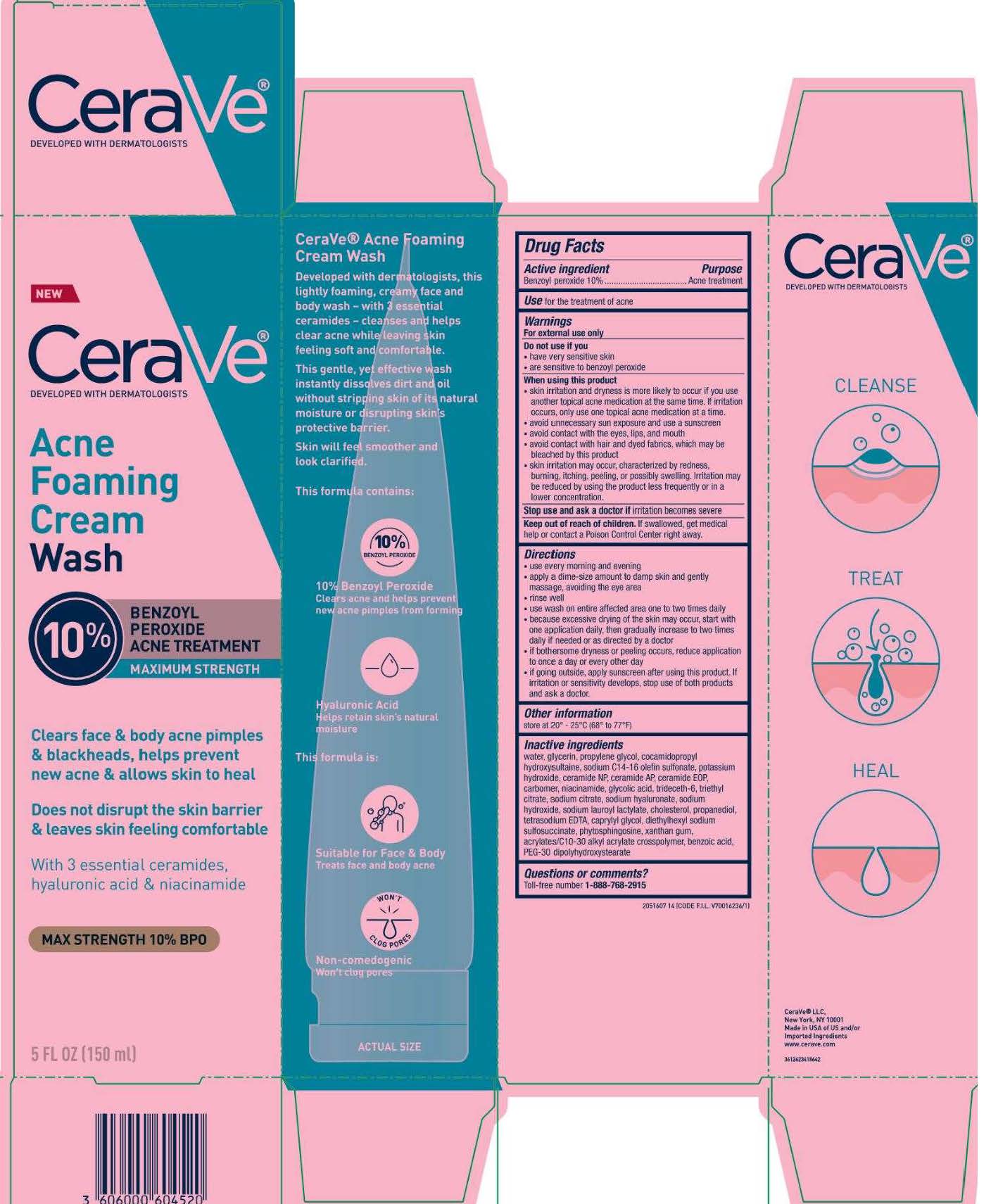 DRUG LABEL: CeraVe Acne Foaming CreamWash
NDC: 49967-604 | Form: CREAM
Manufacturer: L'Oreal USA Products Inc
Category: otc | Type: HUMAN OTC DRUG LABEL
Date: 20240109

ACTIVE INGREDIENTS: BENZOYL PEROXIDE 100 mg/1 mL
INACTIVE INGREDIENTS: WATER; GLYCERIN; PROPYLENE GLYCOL; COCAMIDOPROPYL HYDROXYSULTAINE; SODIUM C14-16 OLEFIN SULFONATE; POTASSIUM HYDROXIDE; CERAMIDE NP; CERAMIDE AP; CERAMIDE 1; CARBOMER HOMOPOLYMER, UNSPECIFIED TYPE; NIACINAMIDE; GLYCOLIC ACID; SODIUM CHLORIDE; TRIDECETH-6; TRIETHYL CITRATE; SODIUM CITRATE; HYALURONATE SODIUM; SODIUM HYDROXIDE; SODIUM LAUROYL LACTYLATE; CHOLESTEROL; PROPANEDIOL; EDETATE SODIUM; CAPRYLYL GLYCOL; DOCUSATE SODIUM; PHYTOSPHINGOSINE; XANTHAN GUM; ACRYLATES/C10-30 ALKYL ACRYLATE CROSSPOLYMER (60000 MPA.S); BENZOIC ACID; PEG-30 DIPOLYHYDROXYSTEARATE

Drug Facts

Active ingredient

Benzoyl peroxide 10%

Purpose

Acne treatment

Use

for the treatment of acne

Warnings

For external use only

Do not use if you

- have very sensitive skin
- are sensitive to benzoyl peroxide

When using this product

• skin irritation and dryness is more likely to occur if you use another topical acne medication at the same time. If irritation occurs, only use one topical acne medication at a time.
• avoid unnecessary sun exposure and use a sunscreen
• avoid contact with the eyes, lips and mouth
• avoid contact with hair and dyed fabrics, which may be bleached by this product
• skin irritation may occur, characterized by redness, burning, itching, peeling or possibly swelling. Irritation may be reduced by using the product less frequently or in a lower concentration.

Stop use and ask a doctor if

skin irritation becomes severe

Keep out of reach of children.

If swallowed, get medical help or contact a Poison Control Center right away.

Directions

• use every morning and evening
• apply a dime-size amount to damp skin and gently massage, avoiding the eye area
• rinse well
• use wash on entire affected area one to two times daily
• because excessive drying of the skin may occur, start with one application daily, then gradually increase to two or three times daily if needed or as directed by a doctor
• if bothersome dryness or peeling occurs, reduce application to once a day or every other day
• if going outside, apply sunscreen after using this product. If irritation or sensitivity develops, stop use of both products and ask a doctor.

Inactive ingredients

water, glycerin, propylene glycol, cocamidopropyl hydroxysultaine, sodium c14-16 olefin sulfonate, potassium hydroxide, ceramide NP, ceramide AP, ceramide EOP, carbomer, , niacinamide, glycolic acid, trideceth-6, triethyl citrate, sodium citrate, sodium hyaluronate, sodium hydroxide, sodium lauroyl lactylate, cholesterol, propanediol, tetrasodium EDTA, caprylyl glycol, diethylhexyl sodium sulfosuccinate, phytosphingosine, xanthan gum, acrylates/c10-30 alkyl acrylate crosspolymer, benzoic acid, PEG-30 dipolyhydroxystearate

Other information

store at 20° - 25°C (68° to 77°F)

Questions orcomments?

Toll-free number 1-888-768-2915